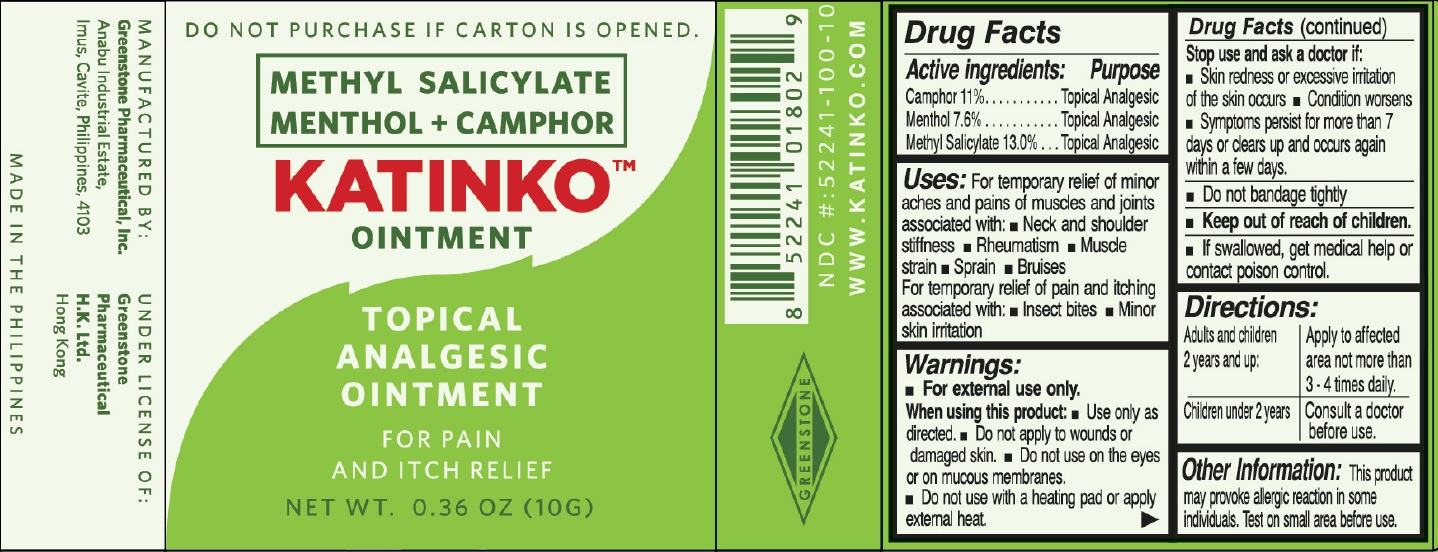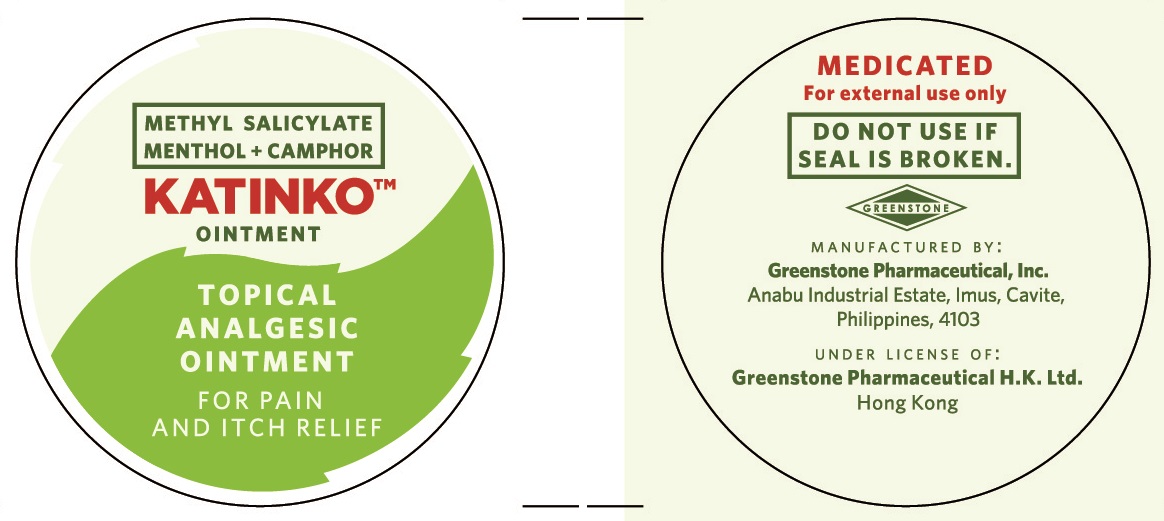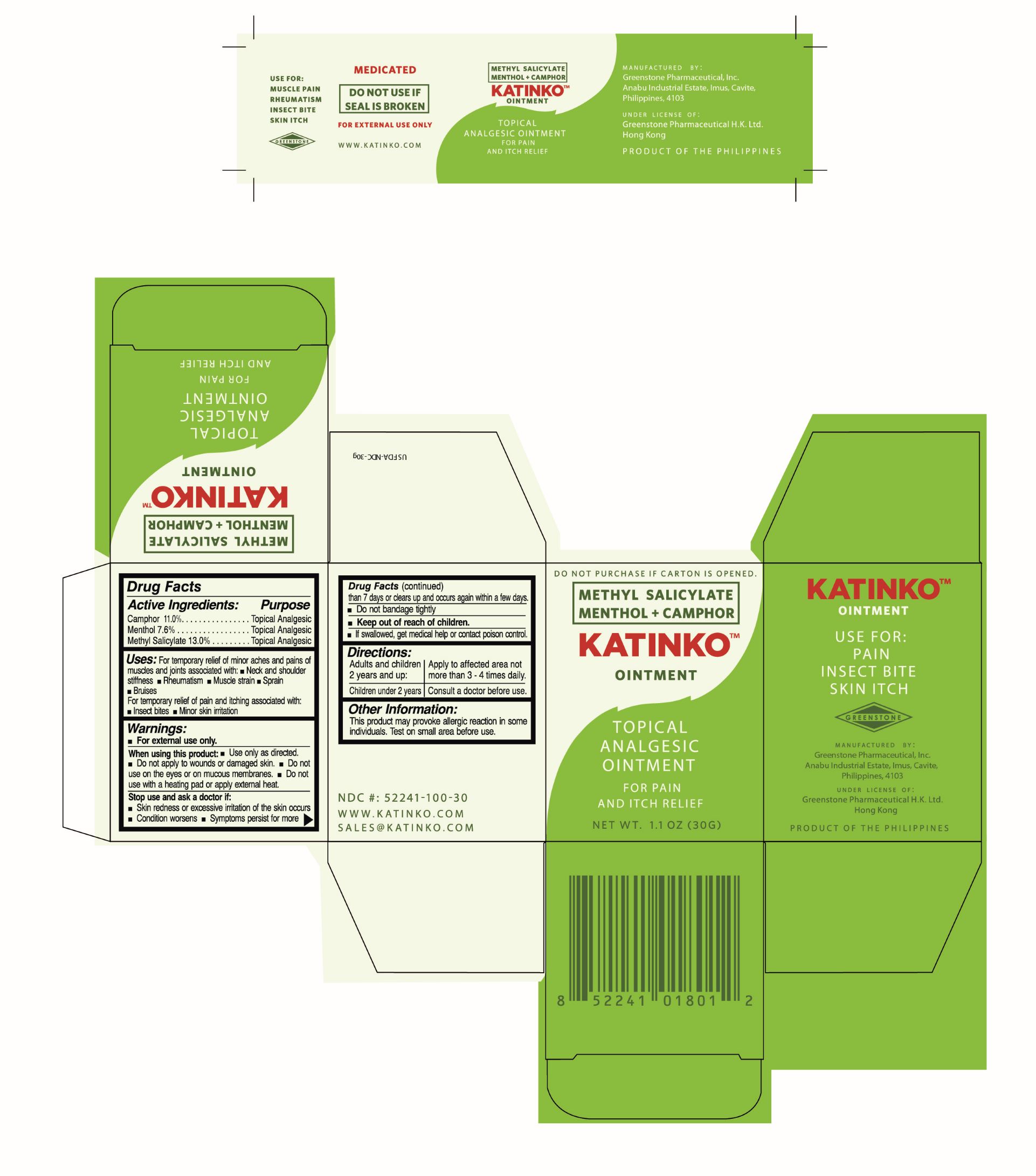 DRUG LABEL: Katinko Pain And Itch Relieving
NDC: 52241-100 | Form: OINTMENT
Manufacturer: Greenstone Pharmaceutical Inc.
Category: otc | Type: HUMAN OTC DRUG LABEL
Date: 20231208

ACTIVE INGREDIENTS: CAMPHOR (SYNTHETIC) 11 g/100 g; MENTHOL 7.6 g/100 g; METHYL SALICYLATE 13 g/100 g
INACTIVE INGREDIENTS: PETROLATUM; PARAFFIN; EUCALYPTUS OIL

Katinko Pain And Itch Relieving Ointment

Active Ingredients:

Camphor 11 percent

Menthol 7.6 percent

Methyl Salicylate 13.0 percent

Purpose

Topical Analgesic

Topical Analgesic

Topical Analgesic

Uses:

For temporary relief of minor aches and pains of muscles and joints associated with:

Simple Backache Arthritis Rheumatism Muscle Strain Sprains Bruises

For temporary relief of pain and itching associated with:

Insect Bites Minor skin irritation

Warnings

For External Use Only.

When using this product:

Use only as directed.

Do not apply to wounds or damaged skin.

Do not use on the eyes or on the mucous membranes.

Do not use with a heating pad or apply external heat.

Stop use and ask a doctor if:

Skin redness or excessive irritation of the skin occurs

Condition worsens

Symptoms persists for more than 7 days or clears up and occurs again within a few days

Do not bandage tightly

Keep out of reach of children

If swallowed, get medical help or contact a poison control

Directions:

Adults and children 2 yrs and up Apply to affected areas not more than 3 to 4 times daily

Children under 2 years Consult a doctor before use

Other Information

This product make provoke allergic reaction in some individuals. Test on small area before use.

Inactive Ingredients

Petroleum Jelly, Paraffin Wax

MANUFACTURED BY:

Greenstone

Pharmaceutical

H.K. Inc.

Anabu Industrial Estate,

Imus, Cavite, Philippines 4103

PRODUCT O F THE PHI L I P PI N E S

MEDICATED

For external use only